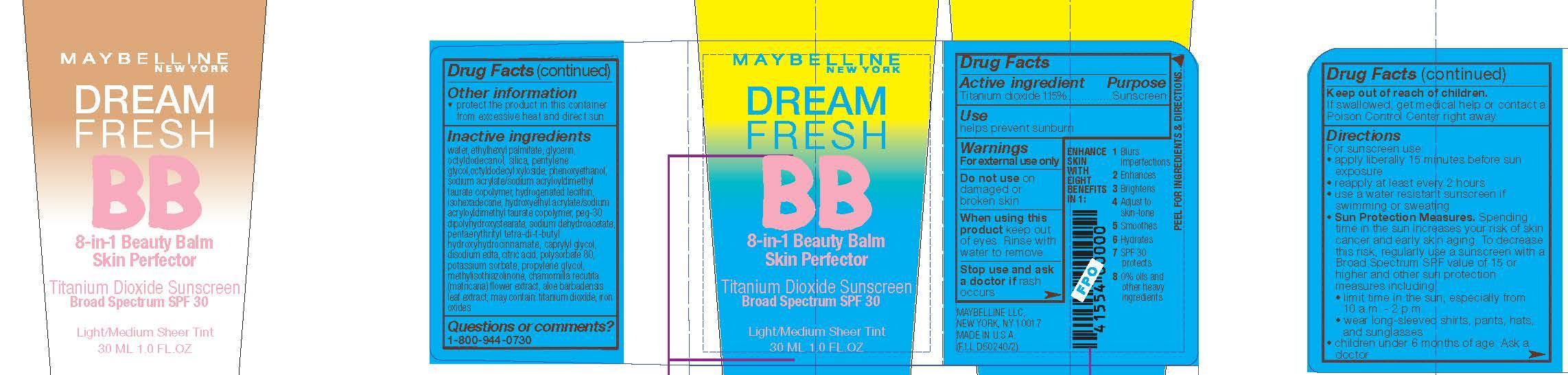 DRUG LABEL: Maybelline New York Dream Fresh BB Beauty Balm Skin Perfector Broad Spectrum SPF 30 Sunscreen
NDC: 49967-264 | Form: CREAM
Manufacturer: L'Oreal USA Products Inc
Category: otc | Type: HUMAN OTC DRUG LABEL
Date: 20240628

ACTIVE INGREDIENTS: TITANIUM DIOXIDE 11.5 mg/1 mL
INACTIVE INGREDIENTS: WATER; GLYCERIN; PENTYLENE GLYCOL

Drug Facts

Active ingredient

Titanium dioxide 1.15%

Purpose

Sunscreen

Use

helps prevent sunburn

Warnings

For external use only

Do not use

on damaged or broken skin

When using this product

keep out of eyes. Rinse with water to remove.

Stop use and ask a doctor if

rash occurs

Keep out of reach of children.

If swallowed, get medical help or contact a Poison Control Center right away.

Directions

For sunscreen use:

● apply liberally 15 minutes before sun exposure

● reapply at least every 2 hours

● use a water resistant sunscreen if swimming or sweating

● Sun Protection Measures. Spending time in the sun increases your risk of skin cancer and early skin aging. To decrease this risk, regularly use a sunscreen with a Broad Spectrum SPF value of 15 or higher and other sun protection measures including:

● limit time in the sun, especially from 10 a.m. – 2 p.m.

● wear long-sleeved shirts, pants, hats, and sunglasses

● children under 6 months of age: Ask a doctor

Other information

protect the product in this container from excessive heat and direct sun

Inactive ingredients

water, ethylhexyl palmitate, glycerin, octyldodecanol, silica, pentylene glycol, octyldodecyl xyloside, phenoxyethanol, sodium acrylate/sodium acryloyldimethyl taurate copolymer, hydrogenated lecithin, isohexadecane, hydroxyethyl acrylate/sodium acryloyldimethyl taurate copolymer, PEG-30 dipolyhydroxystearate, sodium dehydroacetate, pentaerythrityl tetra-di-t-butyl hydroxyhydrocinnamate, caprylyl glycol, disodium EDTA, citric acid, polysorbate 80, potassium sorbate, propylene glycol, methylisothiazolinone, chamomilla recutita (matricaria) flower extract, aloe barbadensis leaf extract; may contain: titanium dioxdie, iron oxides

Questions or comments?

1-800-944-0730